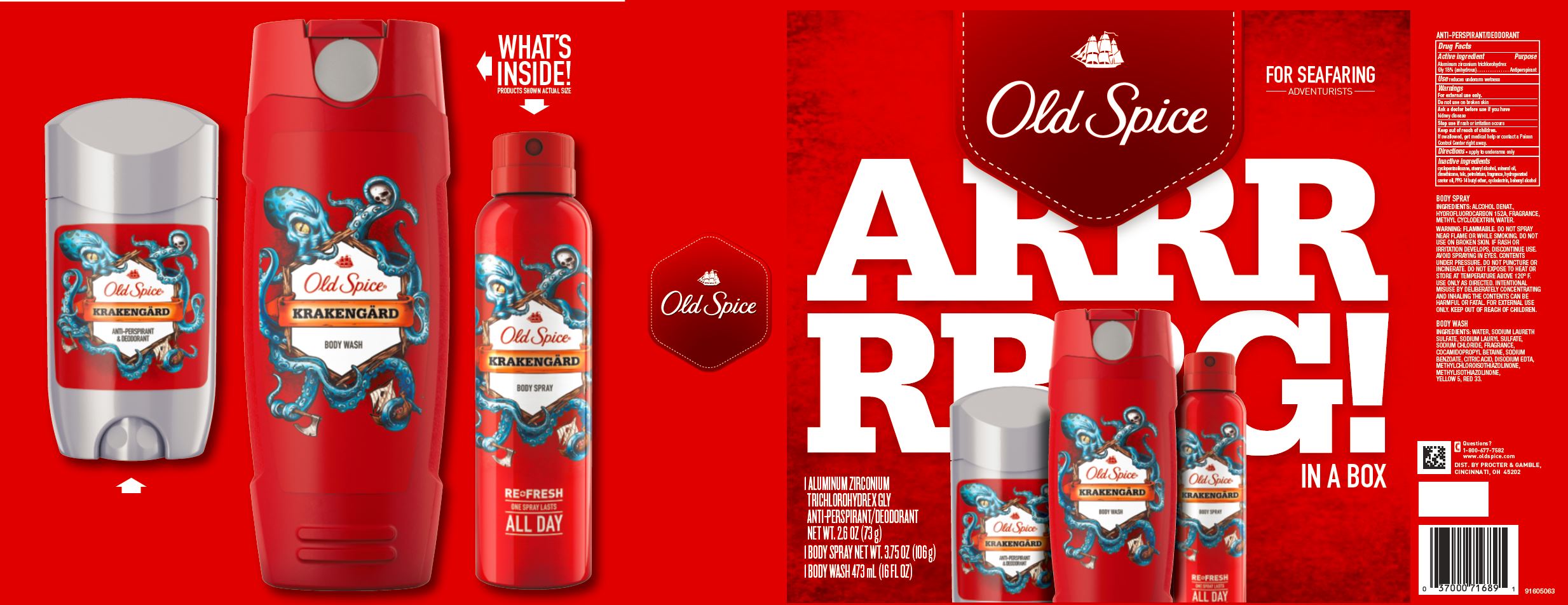 DRUG LABEL: Old Spice Arrrrrrg In A Box Krakengard
NDC: 69423-257 | Form: KIT | Route: TOPICAL
Manufacturer: The Procter & Gamble Manufacturing Company
Category: otc | Type: HUMAN OTC DRUG LABEL
Date: 20200131

ACTIVE INGREDIENTS: ALUMINUM ZIRCONIUM TRICHLOROHYDREX GLY 18 g/100 g
INACTIVE INGREDIENTS: DOCOSANOL; DIMETHICONE; PETROLATUM; PPG-14 BUTYL ETHER; CYCLOMETHICONE 5; STEARYL ALCOHOL; MINERAL OIL; TALC; CASTOR OIL; BETADEX

Old Spice Arrrrrrg In a Box Krakengard

ANTI-PERSPIRANT & DEODORANT

Drug Facts

ACTIVE INGREDIENT

Active ingredients | Purpose
Aluminum zirconium trichlorohydrex Gly 18% (anhydrous) | Antiperspirant

Use

Reduces underarm wetness

Warnings

For external use only

Do not use on broken skin

Ask a doctor before use if you have kidney disease

Stop use if rash or irritation occurs

Keep out of reach of children. If swallowed, get medical help or contact a Poison Control Center right away.

Directions

apply to underarms only

Inactive ingredients

cyclopentasiloxane, stearyl alcohol, mineral oil, dimethicone, talc, petrolatum, hydrogenated castor oil, fragrance, PPG-14 butyl ether, cyclodextrin, behenyl alcohol

Questions or comments?

1-800-677-7582

www.oldspice.com

Old Spice Wild Collection Krakengardi Body Wash (Cosmetic)

INGREDIENTS:

WATER, SODIUM LAURETH SULFATE, SODIUM LAURYL SULFATE, SODIUM CHLORIDE, FRAGRANCE, COCAMIDOPROPYL BETAINE, SODIUM BENZOATE, CITRIC ACID, DISODIUM EDTA, METHYLCHLOROISOTHIAZOLINONE,

METHYLISOTHIAZOLINONE, YELLOW 5, RED 33.

Old Spice Wild Collection Krakengard Body Spray (Cosmetic)

INGREDIENTS

ALCOHOL DENAT., HYDROFLUOROCARBON 152A, FRAGRANCE, METHYL CYCLODEXTRIN,WATER.

Dist. by PROCTER & GAMBLE,
CINCINNATI, OH 45202

PRINCIPAL DISPLAY PANEL - Kit Carton

Old Spice

ARRRRRRG! IN A BOX

1 ALUMINUM ZIRCONIUM TRICHLOROHYDREX GLY ANTI-PERSPIRANT/DEODORANT NET WT. 2.6 OZ (73 g)

1 BODY WASH 473 mL (16 FL OZ) • 1 BODY SPRAY NET WT. 3.75 OZ (106 g)